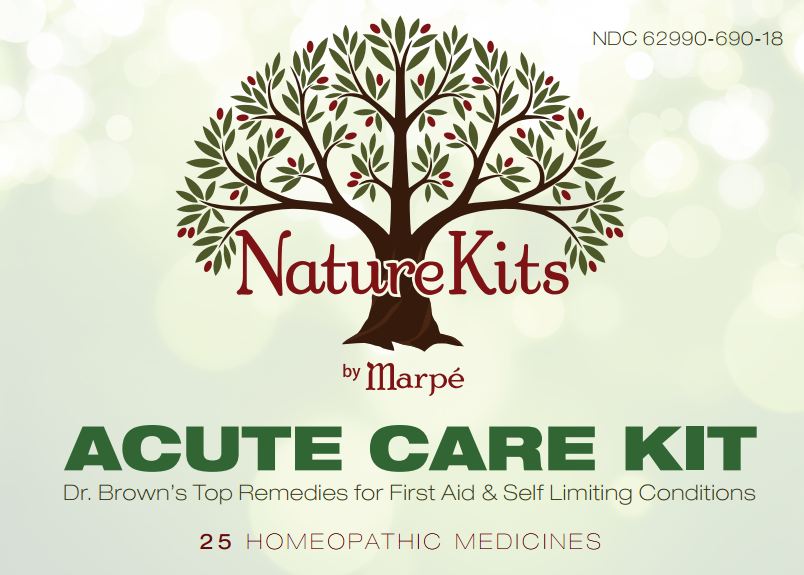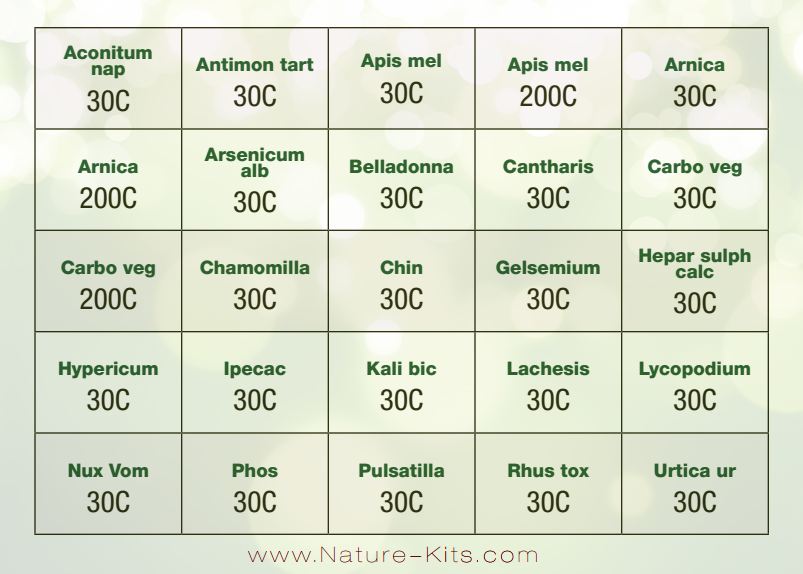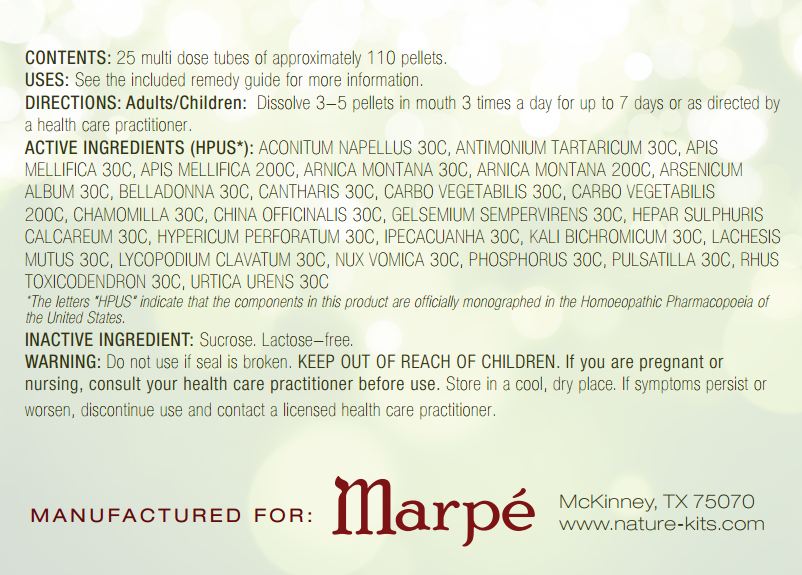 DRUG LABEL: Acute Care Kit
NDC: 62990-690 | Form: PELLET
Manufacturer: MARPE LLC
Category: homeopathic | Type: HUMAN OTC DRUG LABEL
Date: 20140430

ACTIVE INGREDIENTS: ACONITUM NAPELLUS 30 [hp_C]/1 1; ANTIMONY POTASSIUM TARTRATE 30 [hp_C]/1 1; APIS MELLIFERA 30 [hp_C]/1 1; ARNICA MONTANA 30 [hp_C]/1 1; ARSENIC TRIOXIDE 30 [hp_C]/1 1; ATROPA BELLADONNA 30 [hp_C]/1 1; LYTTA VESICATORIA 30 [hp_C]/1 1; ACTIVATED CHARCOAL 30 [hp_C]/1 1; MATRICARIA RECUTITA 30 [hp_C]/1 1; CINCHONA OFFICINALIS BARK 30 [hp_C]/1 1; GELSEMIUM SEMPERVIRENS ROOT 30 [hp_C]/1 1; CALCIUM SULFIDE 30 [hp_C]/1 1; HYPERICUM PERFORATUM 30 [hp_C]/1 1; IPECAC 30 [hp_C]/1 1; POTASSIUM DICHROMATE 30 [hp_C]/1 1; LACHESIS MUTA VENOM 30 [hp_C]/1 1; LYCOPODIUM CLAVATUM SPORE 30 [hp_C]/1 1; STRYCHNOS NUX-VOMICA SEED 30 [hp_C]/1 1; PHOSPHORUS 30 [hp_C]/1 1; PULSATILLA VULGARIS 30 [hp_C]/1 1; TOXICODENDRON PUBESCENS LEAF 30 [hp_C]/1 1; URTICA URENS 30 [hp_C]/1 1
INACTIVE INGREDIENTS: SUCROSE

ACUTE CARE KIT

ACTIVE INGREDIENT

ACTIVE INGREDIENTS (HPUS*): ACONITUM NAPELLUS 30C, ANTIMONIUM TARTARICUM 30C, APIS MELLIFICA 30C, APIS MELLIFICA 200C, ARNICA MONTANA 30C, ARNICA MONTANA 200C, ARSENICUM ALBUM 30C, BELLADONNA 30C, CANTHARIS 30C, CARBO VEGETABILIS 30C, CARBO VEGETABILIS 200C, CHAMOMILLA 30C, CHINA OFFICINALIS 30C, GELSEMIUM SEMPERVIRENS 30C, HEPAR SULPHURIS CALCAREUM 30C, HYPERICUM PERFORATUM 30C, IPECACUANHA 30C, KALI BICHROMICUM 30C, LACHESIS MUTUS 30C, LYCOPODIUM CLAVATUM 30C, NUX VOMICA 30C, PHOSPHORUS 30C, PULSATILLA 30C, RHUS TOXICODENDRON 30C, URTICA URENS 30C.

OTHER SAFETY INFORMATION

* The letters “HPUS” indicate that the components in this product are officially monographed in the Homoeopathic Pharmacopoeia of the United States.

INDICATIONS AND USAGE

USES: See the included remedy guide for more information.

DOSAGE AND ADMINISTRATION

DIRECTIONS: Adults/Children: Dissolve 3-5 pellets in mouth 3 times a day for up to 7 days or as directed by a health care practitioner.

WARNING:
Do not use if seal is broken. If you are pregnant or nursing, consult your health care practitioner before use. Store in a cool, dry place. If symptoms persist or worsen, discontinue use and contact a licensed health care practitioner.

KEEP OUT OF THE REACH OF CHILDREN.

INACTIVE INGREDIENT: Sucrose. Lactose - free.

QUESTIONS

MANUFACTURED FOR:

MARPE

McKinney, TX 75070

www.nature-kits.com

PACKAGE LABEL

- NDC: 62990-690-18

Nature Kits by Marpe
ACUTE CARE KIT
Dr. Brown's Top Remedies for First Aid and Self Limiting Conditions

- 25 HOMEOPATHIC MEDICINES

PURPOSE

Dr. Brown's Top Remedies for First Aid and Self Limiting Conditions